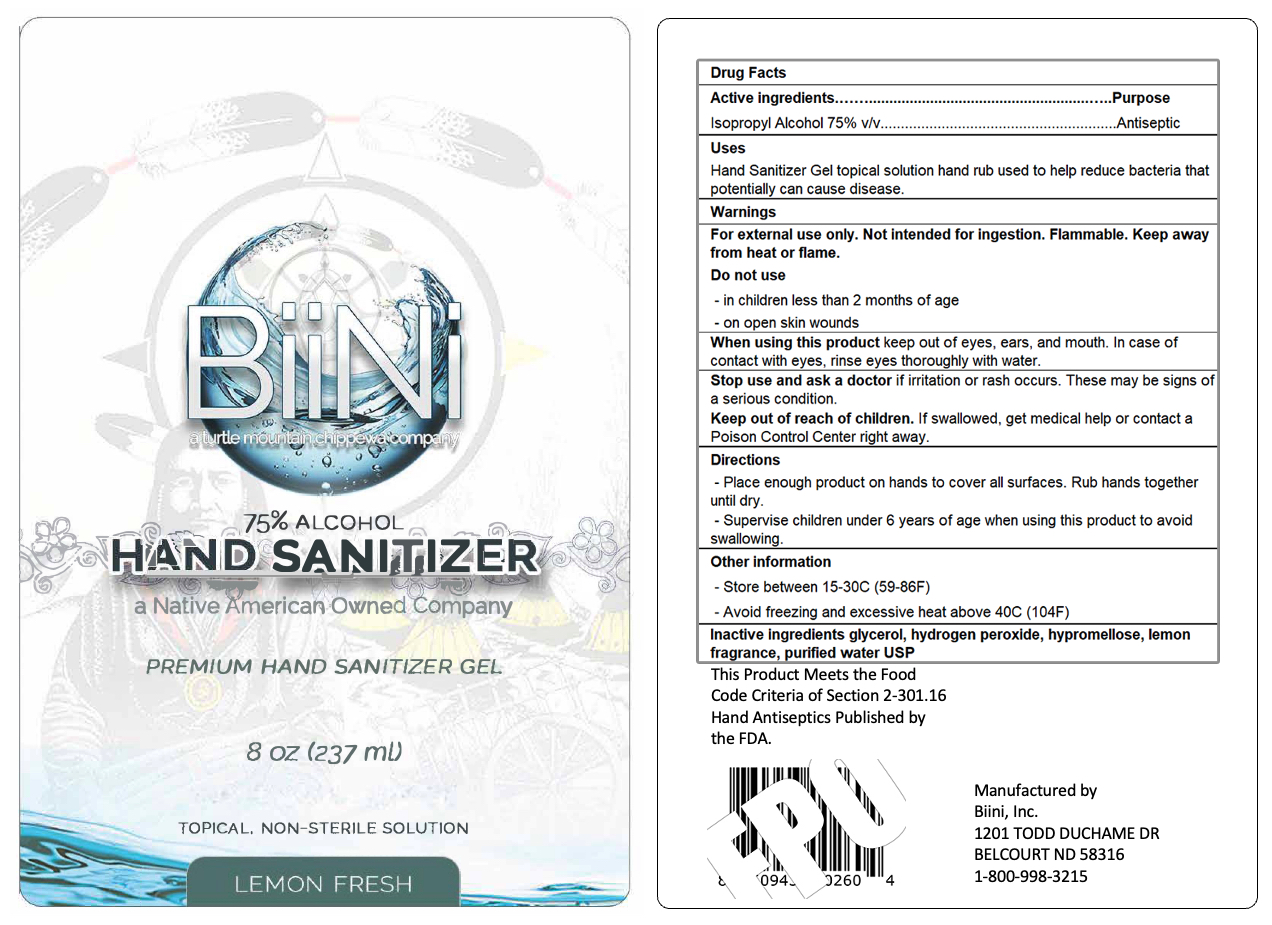 DRUG LABEL: BiiNi Hand Sanitizer
NDC: 83156-562 | Form: GEL
Manufacturer: Biini, Inc.
Category: otc | Type: HUMAN OTC DRUG LABEL
Date: 20221216

ACTIVE INGREDIENTS: ISOPROPYL ALCOHOL 0.07 mL/1 mL
INACTIVE INGREDIENTS: LEMON; GLYCERIN; WATER; ACRYLATES/VINYL ISODECANOATE CROSSPOLYMER (10000 MPA.S NEUTRALIZED AT 0.5%)

ACTIVE INGREDIENT

Isopropyl Alcohol 75% v/v Purpose Antiseptic

PURPOSE

Antiseptic

INDICATIONS AND USAGE

Hand sanitizer to help reduce bacteria that potentially can cause diseases

WARNINGS

For external use only. Not intended for ingestion. Flammable. Keep away from fire or flame.

DO NOT USE

- on open skin wounds
- in children less than 2 months of age

WHEN USING

Keep out of eyes, ears, and mouth. In case of contact with eyes, rinse eyes thoroughly with water.

INACTIVE INGREDIENT

glycerin, lemon fragrance, PEG-6 AMP-acrylates/ vinyl isodecanoate crosspolymer, purified water USP

STORAGE AND HANDLING

- store between 15-30C (59-86F)
- avoid freezing and excessive heat above 40C (104F)

DOSAGE AND ADMINISTRATION

- place enough product on hands to cover all surfaces and rub together until dry
- supervise children under 6 years of age when using product to avoid swallowing

KEEP OUT OF REACH OF CHILDREN

If swallowed, get medical help or contact a Poison Control Center right away.

STOP USE

and ask a doctor if irritation or rash occurs. These may be signs of a serious condition.

The hand sanitizer is manufactured using only the following United States Pharmacopoeia (USP) grade ingredients in the preparation of the product (percentage in final product formulation) consistent with World Health Organization (WHO) recommendations:

Isopropyl Alcohol (75%, v/v) in an aqueous solution denatured according to Alcohol and Tobacco Tax and Trade Bureau regulations in 27 CFR part 20.
Glycerol (1.45% v/v).
Hydrogen peroxide (0.125% v/v).
Sterile distilled water or boiled cold water.
The firm does not add other active or inactive ingredients. Different or additional ingredients may impact the quality and potency of the product.